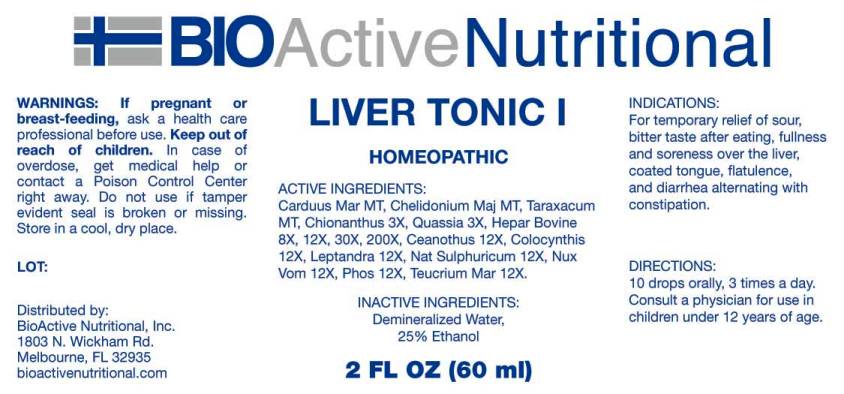 DRUG LABEL: LIVER TONIC
NDC: 43857-0345 | Form: LIQUID
Manufacturer: BioActive Nutritional, Inc.
Category: homeopathic | Type: HUMAN OTC DRUG LABEL
Date: 20170228

ACTIVE INGREDIENTS: MILK THISTLE 1 [hp_X]/1 mL; CHELIDONIUM MAJUS 1 [hp_X]/1 mL; TARAXACUM OFFICINALE 1 [hp_X]/1 mL; CHIONANTHUS VIRGINICUS BARK 3 [hp_X]/1 mL; QUASSIA AMARA WOOD 3 [hp_X]/1 mL; BEEF LIVER 8 [hp_X]/1 mL; CEANOTHUS AMERICANUS LEAF 12 [hp_X]/1 mL; CITRULLUS COLOCYNTHIS FRUIT PULP 12 [hp_X]/1 mL; VERONICASTRUM VIRGINICUM ROOT 12 [hp_X]/1 mL; SODIUM SULFATE 12 [hp_X]/1 mL; STRYCHNOS NUX-VOMICA SEED 12 [hp_X]/1 mL; PHOSPHORUS 12 [hp_X]/1 mL; TEUCRIUM MARUM 12 [hp_X]/1 mL
INACTIVE INGREDIENTS: WATER; ALCOHOL

Drug Facts:

ACTIVE INGREDIENTS:

Carduus Marianus MT, Chelidonium Majus MT, Taraxacum Officinale MT, Chionanthus Virginica 3X, Quassia (Amara) 3X, Hepar Bovine 8X, 12X, 30X, 200X, Ceanothus Americanus 12X, Colocynthis 12X, Leptandra Virginica 12X, Natrum Sulphuricum 12X, Nux Vomica 12X, Phosphorus 12X, Teucrium Marum 12X.

INDICATIONS:

For temporary relief of sour, bitter taste after eating, fullness and soreness over the liver, coated tongue, flatulence and diarrhea alternating with constipation.

WARNINGS:

If pregnant or breast-feeding, ask a health care professional before use.

Keep out of reach of children. In case of overdose, get medical help or contact a Poison Control Center right away.

Do not use if tamper evident seal is broken or missing.

Store in cool, dry place.

Keep out of reach of children. In case of overdose, get medical help or contact a Poison Control Center right away.

DIRECTIONS:

10 drops orally, 3 times a day. Consult a physician for use in children under 12 years of age.

INDICATIONS:

For temporary relief of sour, bitter taste after eating, fullness and soreness over the liver, coated tongue, flatulence and diarrhea alternating with constipation.

INACTIVE INGREDIENTS:

Demineralized Water, 25% Ethanol.

QUESTIONS:

Distributed by:
BioActive Nutritional, Inc.
1803 N. Wickham Rd.
Melbourne, FL 32935
bioactivenutritional.com

PACKAGE LABEL DISPLAY:

BIOActive Nutritional

LIVER TONIC I

HOMEOPATHIC

2 FL OZ (60 ml)